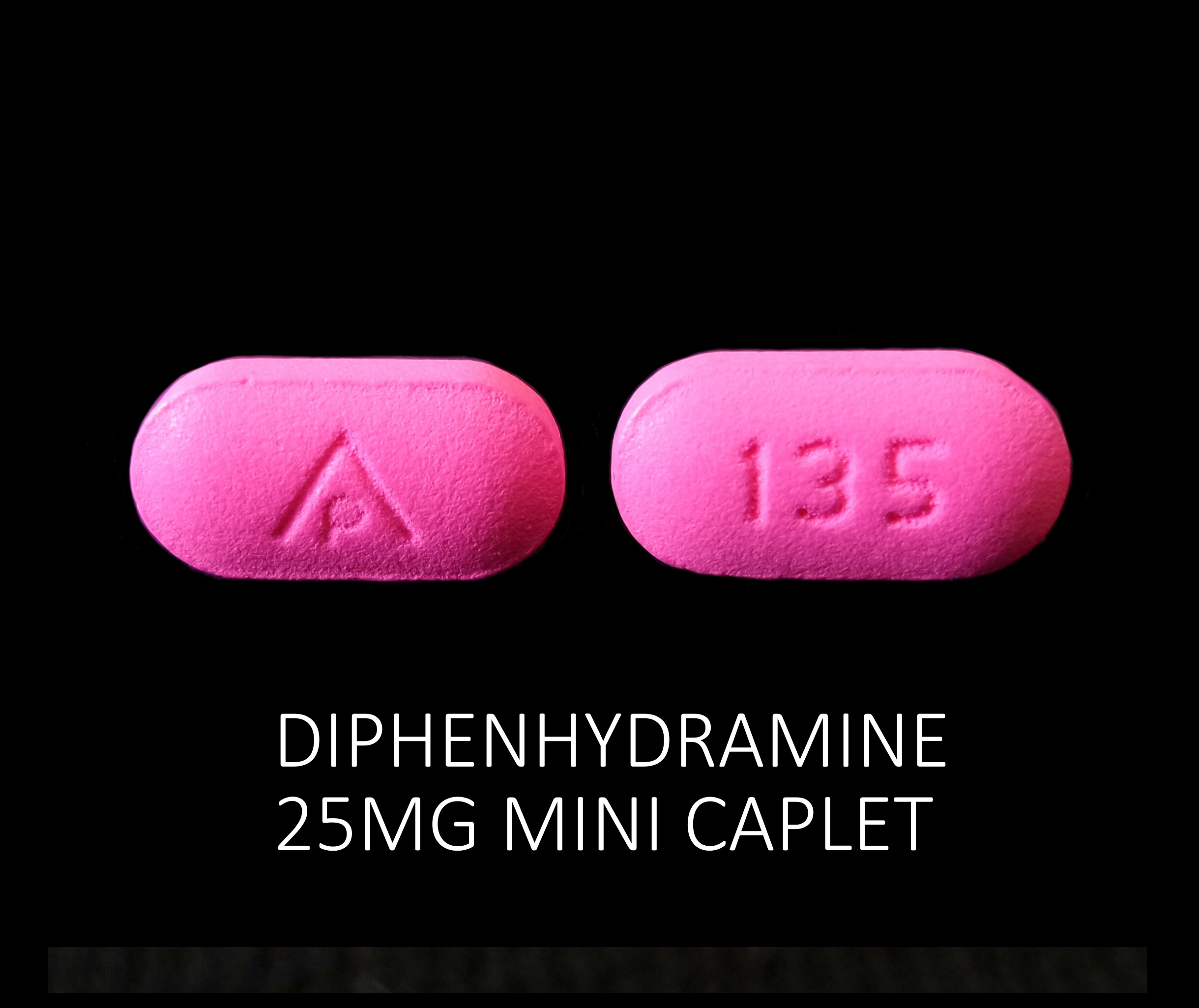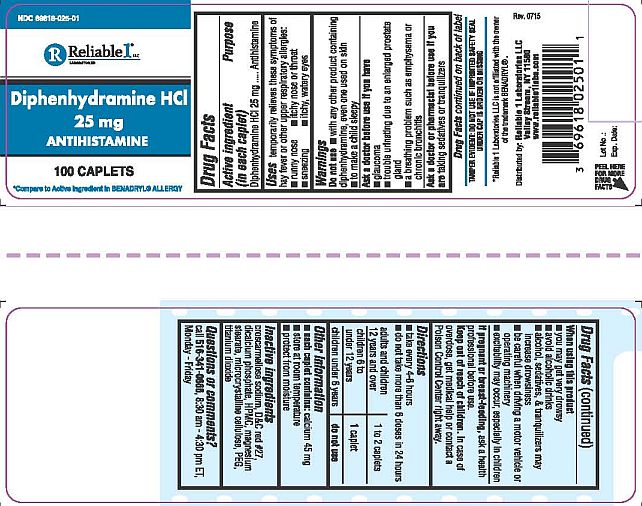 DRUG LABEL: Diphenhydramine HCL 25 mg
NDC: 69618-025 | Form: TABLET
Manufacturer: Reliable 1 Laboratories LLC
Category: otc | Type: HUMAN OTC DRUG LABEL
Date: 20250115

ACTIVE INGREDIENTS: DIPHENHYDRAMINE HYDROCHLORIDE 25 mg/1 1
INACTIVE INGREDIENTS: CROSCARMELLOSE SODIUM; D&C RED NO. 27; CELLULOSE, MICROCRYSTALLINE; HYPROMELLOSES; MAGNESIUM STEARATE; DIBASIC CALCIUM PHOSPHATE DIHYDRATE; POLYETHYLENE GLYCOL 1000; TITANIUM DIOXIDE

Diphenhydramine HCL 25 mg Caplets

Drug Facts

Active ingredient (in each caplet)

Diphenhydramine HCL 25 mg

Purpose

Antihistamine

Uses

temporarily relieves these symptoms of hay fever or other upper respiratory allergies:

- runny nose
- sneezing
- itchy nose or throat
- itchy, watery eyes

Warnings

Do not use

- with any other product containing diphenhydramine, even one use on skin
- to make a child sleepy

Ask a doctor before use if you have

- glaucoma
- trouble urinating due to an enlarged prostate gland
- a breating problem such as emphysema or chronic bronchitis

Ask a doctor or pharmacist before use if you are taking sedatives or tranquilizers

Drug Facts continued on back of label

When using this product

- you may get very drowsy
- avoid alcoholic drinks
- alcohol, sedatives, & tranquilizers may increase drowsiness
- be careful when driving a motor vehicle or operating machinery
- excitability may occur, especially in children

PREGNANCY OR BREAST FEEDING

If pregnant or breat-feeding, ask a health professional before use.

Keep out of reach of children. In case of overdose, get medical helo or contact a Poison Control Center right away.

Directions

- take every 4-6 hours
- do not take more than 6 doses in 24 hours

adults and children 12 years and over | 1 to 2 caplets
children 6 to under 12 years | 1 caplet
children under 6 years | do not use

Other information

- each caplet contains: calcium 45 mg
- store at room temperature
- protect from moisture

Inactive ingredients

croscarmellose sodium, D&C red #27, dicalcium phosphate, HPMC, magnesium stearate, microcrystalline cellulose, PEG, titanium dioxide

Questions or comments?

call 516-341-0666, 8:30 am - 4:30 pmET, Monday - Friday

TAMPER EVIDENT: DO NOT USE IF IMPRINTED SAFETY SEAL UNDER CAP IS BROKEN OR MISSING

*Reliable 1 Laboratories LLC is not affiliated with the owner of the trademark BENADRYL®

Distributed by: Reliable 1 Laboratories LLC

Valley Stream, NY 11580

www.reliable1labs.com

PACKAGE LABEL

NDC 69618-025-01

Diphenhydramine HCL 25 mg

ANTIHISTAMINE

100 CAPLETS

*Compare to Active Ingredient in BENADRYL® ALLERGY